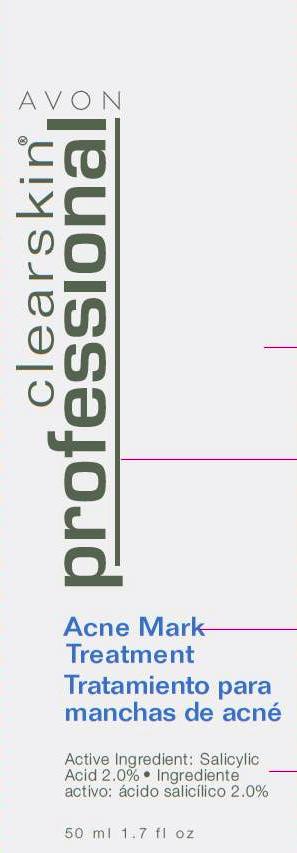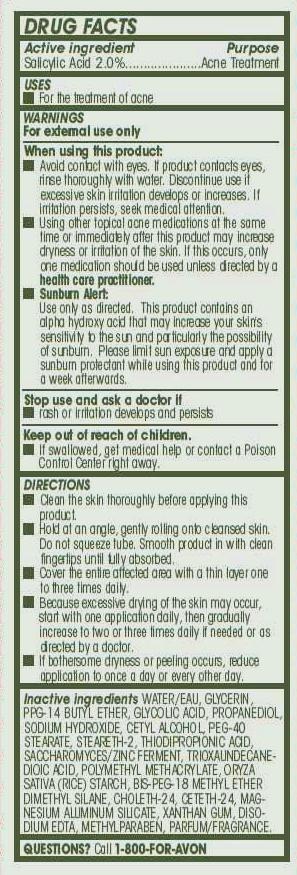 DRUG LABEL: Clearskin Professional
NDC: 10096-0264 | Form: CREAM
Manufacturer: Avon Products, Inc.
Category: otc | Type: HUMAN OTC DRUG LABEL
Date: 20110928

ACTIVE INGREDIENTS: SALICYLIC ACID	 1 mL/50 mL

Drug Facts

Active ingredient
Salicylic Acid 2.0%.....................

Purpose
............Acne Treatment

USES

- For the treatment of acne

WARNINGS
For external use only

When using this product:

- Avoid contact with eyes. If product contacts eyes, rinse thoroughly with water. Discontinue use if excessive skin irritation develops or increases. If irritation persists, seek medical attention.

- Using other topical acne medications at the same time or immediately after this product may increase dryness or irritation of the skin. If this occurs, only one medication should be used unless directed by a health care practitioner.

- Sunburn Alert: Use only as directed. This product contains an alpha hydroxy acid that may increase your skin's sensitivity to the sun and particularly the possibility of sunburn. Please limit sun exposure and apply a sunburn protectant while using this product and for a week afterwards.

Stop use and ask a doctor if

- rash or irritation develops and persists

Keep out of reach of children.

- If swallowed, get medical help or contact a Poison Control Center right away.

DIRECTIONS

- Clean the skin thoroughly before applying this product.

- Hold at an angle, gently rolling onto cleansed skin. Do not squeeze tube. Smooth product in with clean fingertips until fully absorbed.

- Cover the entire affected area with a thin layer one to three times daily.

- Because excessive drying of the skin may occur, start with one application daily, then gradually increase to two or three times daily if needed or as directed by a doctor.

- If bothersome dryness or peeling occurs, reduce application to once a day or every other day.

INACTIVE INGREDIENT

Inactive ingredients WATER/EAU, GLYCERIN, PPG-14 BUTYL ETHER, GLYCOLIC ACID, PROPANEDIOL, SODIUM HYDROXIDE, CETYL ALCOHOL, PEG-40 STEARATE, STEARETH-2, THIODIPROPIONIC ACID, SACCHAROMYCES/ZINC FERMENT, TRIOXAUNDECANEDIOIC ACID, POLYMETHYL METHACRYLATE, ORYZA SATIVA (RICE) STARCH, BIS-PEG-18 METHYL ETHER DIMETHYL SILANE, CHOLETH-24, CETETH-24, MAGNESIUM ALUMINUM SILICATE, XANTHAN GUM, DISODIUM EDTA, METHYLPARABEN, PARFUM/FRAGRANCE.

QUESTIONS? Call 1-800-FOR-AVON